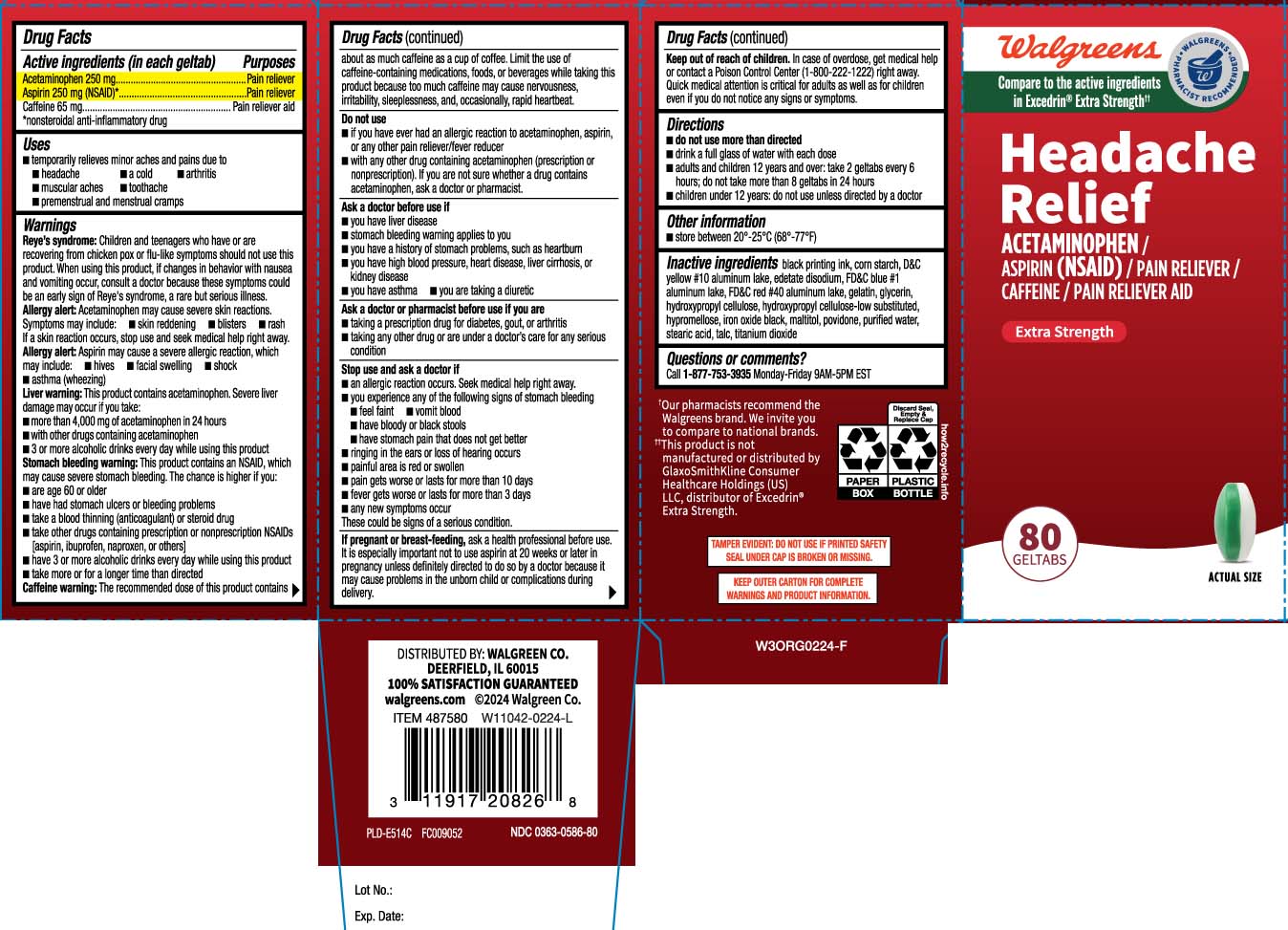 DRUG LABEL: Headache Relief
NDC: 0363-0586 | Form: TABLET
Manufacturer: Walgreens
Category: otc | Type: HUMAN OTC DRUG LABEL
Date: 20251007

ACTIVE INGREDIENTS: ACETAMINOPHEN 250 mg/1 1; ASPIRIN 250 mg/1 1; CAFFEINE 65 mg/1 1
INACTIVE INGREDIENTS: STARCH, CORN; D&C YELLOW NO. 10; EDETATE DISODIUM; FD&C BLUE NO. 1; FD&C RED NO. 40; GELATIN; GLYCERIN; GLYCERYL MONO- AND DICAPRYLOCAPRATE; HYDROXYPROPYL CELLULOSE, UNSPECIFIED; HYPROMELLOSES; FERROSOFERRIC OXIDE; MALTITOL; POVIDONE; WATER; STEARIC ACID; TALC; TITANIUM DIOXIDE; HYDROXYPROPYL CELLULOSE, LOW SUBSTITUTED

Drug Facts

Active ingredients (in each geltab)

Acetaminophen 250 mg

Aspirin 250 mg (NSAID)*

Caffeine 65 mg

*nonsteroidal anti-inflammatory drug

Purposes

Pain reliever

Pain reliever

Pain reliever aid

Uses

- temporarily relieves minor aches and pains due to:
  - headache
  - a cold
  - arthritis
  - muscular aches
  - toothache
  - premenstrual and menstrual cramps

Warnings

Reye's syndrome: Children and teenagers who have or are recovering from chicken pox or flu-like symptoms should not use this product. When using this product, if changes in behavior with nausea and vomiting occur, consult a doctor because these symptoms could be an early sign of Reye’s syndrome, a rare but serious illness

Allergy alert: Acetaminophen may cause severe skin reactions. Symptoms may include:

- skin reddening
- blisters
- rash

If a skin reaction occurs, stop use and seek medical help right away.

Allergy alert: Aspirin may cause a severe allergic reaction, which may include:

- hives
- facial swelling
- shock
- asthma (wheezing)

Liver warning: This product contains acetaminophen. Severe liver damage may occur if you take:

- more than 4,000 mg of acetaminophen in 24 hours
- with other drugs containing acetaminophen
- 3 or more alcoholic drinks every day while using this product

Stomach bleeding warning: This product contains an NSAID, which may cause severe stomach bleeding. The chance is higher if you:

- are age 60 or older
- have had stomach ulcers or bleeding problems
- take a blood thinning (anticoagulant) or steroid drug
- take other drugs containing prescription or nonprescription NSAIDs (aspirin, ibuprofen, naproxen, or others)
- have 3 or more alcoholic drinks every day while using this product
- take more or for a longer time than directed

Caffeine warning: The recommended dose of this product contains about as much caffeine as a cup of coffee. Limit the use of caffeine-containing medications, foods, or beverages while taking this product because too much caffeine may cause nervousness, irritability, sleeplessness, and, occasionally, rapid heartbeat.

Do not use

- if you have ever had an allergic reaction to acetaminophen, aspirin or any other pain reliever/fever reducer
- with any other drug containing acetaminophen (prescription or nonprescription). If you are not sure whether a drug contains acetaminophen, ask a doctor or pharmacist.

Ask a doctor before use if

- you have liver disease
- stomach bleeding warning applies to you
- you have a history of stomach problem, such as heartburn
- you have high blood pressure, heart disease, liver cirrhosis, or kidney disease
- you have asthma
- you are taking a diuretic

Ask a doctor or pharmacist before use if you are

- taking a prescription drug for diabetes, gout, or arthritis
- taking any other drug or are under a doctor’s care for any serious condition

Stop use and ask doctor if

- an allergic reaction occurs. Seek medical help right away.
- you experience any of the following signs of stomach bleeding
  - feel faint
  - vomit blood
  - have bloody or black stools
  - have stomach pain that does not get better
- ringing in the ears or loss of hearing occurs
- painful area is red or swollen
- pain gets worse or lasts for more than 10 days
- fever gets worse or lasts for more than 3 days
- any new symptoms occur.

These could be signs of a serious condition.

If pregnant or breast-feeding,

ask a health professional before use. It is especially important not to use aspirin at 20 weeks or later in pregnancy unless definitely directed to do so by a doctor because it may cause problems in the unborn child or complications during delivery.

Keep out of reach of children.

In case of overdose, get medical help or contact a Poison Control Center (1-800-222-1222) right away. Quick medical attention is critical for adults as well as for children even if you do not notice any signs or symptoms.

Directions

- do not use more than directed
- drink a full glass of water with each dose
- adults and children 12 years and over: take 2 geltabs every 6 hours; do not take more than 8 geltabs in 24 hours
- children under 12 years: do not use unless directed by a doctor

Other information

- store between 20º-25ºC (68º-77ºF)

Inactive ingredients

black printing ink,corn starch, D&C yellow #10 aluminum lake, edetate disodium, FD&C blue #1 aluminum lake, FD&C red #40 aluminum lake, gelatin, glycerin, hydroxypropyl cellulose, hydroxypropyl cellulose-low substituted, hypromellose, iron oxide black, maltitol, povidone, purified water, stearic acid, talc, titanium dioxide

Questions or comments?

Call 1-877-753-3935 Monday-Friday 9AM-5PM EST

Principal Display Panel

Compare to the active ingredients in Excedrin® Extra Strength††

Headache Relief

ACETAMINOPHEN / ASPIRIN (NSAID) / PAIN RELIEVER

CAFFEINE / PAIN RELIEVER AID

Extra Strength

GELTABS

††This product is not manufactured or distributed by GlaxoSmithKline Consumer Healthcare Holdings (US) LLC, distributor of Excedrin® Extra Strength.

TAMPER EVIDENT: DO NOT USE IF PRINTED SAFETY SEAL UNDER CAP IS BROKEN OR MISSING.

KEEP OUTER CARTON FOR COMPLETE WARNINGS AND PRODUCT INFORMATION.

DISTRIBUTED BY: WALGREEN CO.

DEERFIELD, IL 60015

Package Label

WALGREENS Extra Strength Headache Relief